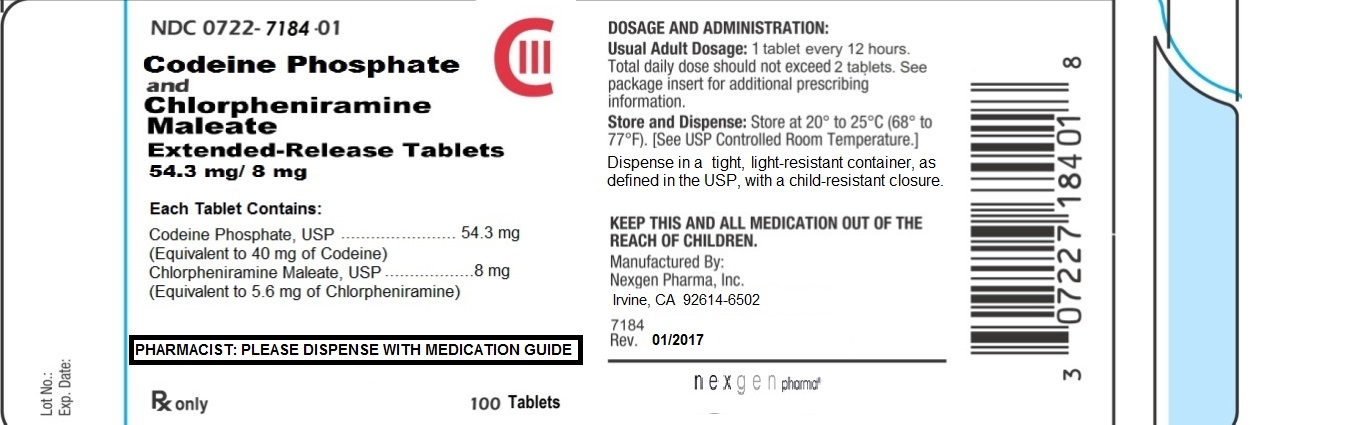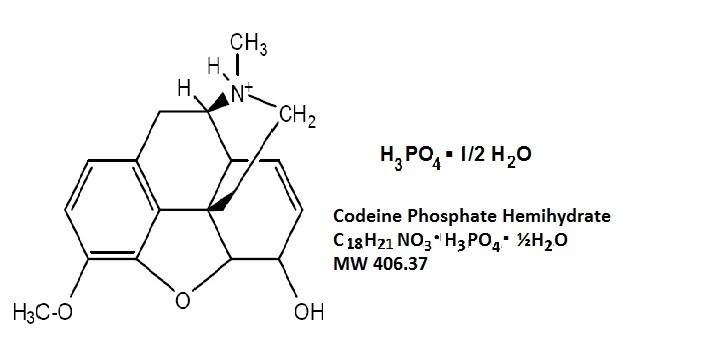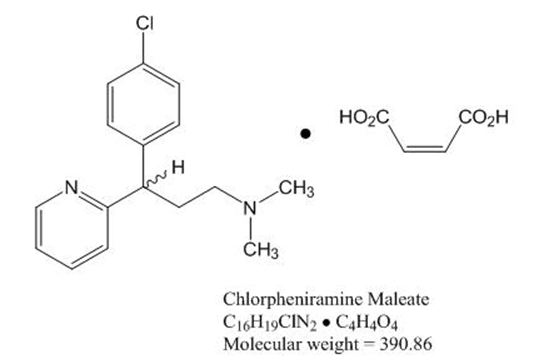 DRUG LABEL: CODEINE AND CHLORPHENIRAMINE MALEATE ER
NDC: 0722-7184 | Form: TABLET, EXTENDED RELEASE
Manufacturer: Nexgen Pharma, Inc.
Category: prescription | Type: HUMAN PRESCRIPTION DRUG LABEL
Date: 20170120
DEA Schedule: CIII

ACTIVE INGREDIENTS: CODEINE PHOSPHATE 54.3 mg/1 1; CHLORPHENIRAMINE MALEATE 8 mg/1 1
INACTIVE INGREDIENTS: HYPROMELLOSE 2208 (4000 MPA.S); LACTOSE MONOHYDRATE; CELLULOSE, MICROCRYSTALLINE; POLYSORBATE 80; MAGNESIUM STEARATE; SILICON DIOXIDE

HIGHLIGHTS OF PRESCRIBING INFORMATION

These highlights do not include all the information needed to use CODEINE PHOSPHATE AND CHLORPHENIRAMINE MALEATE™ safely and effectively. See full prescribing information for CODEINE PHOSPHATE AND CHLORPHENIRAMINE MALEATE.
CODEINE PHOSPHATE AND CHLORPHENIRAMINE MALEATE (codeine phosphate and chlorpheniramine maleate) extended release tablets, CIII
Initial U.S. Approval: 1985

RECENT MAJOR CHANGES

Boxed Warning 1/2017
Warnings and Precautions (5.2) 1/2017

WARNINGDEATH RELATED TO ULTRA-RAPID METABOLISM OF CODEINE TO MORPHINE and RISKS FROM CONCOMITANT USE WITH BENZODIAZEPINES OR OTHER CNS DEPRESSANTS

WARNING

DEATH RELATED TO ULTRA-RAPID METABOLISM OF CODEINE TO MORPHINE and

RISKS FROM CONCOMITANT USE WITH BENZODIAZEPINES OR OTHER CNS DEPRESSANTS

Ultra-Rapid Metabolism

Respiratory depression and death have occurred in children who received codeine following tonsillectomy and/or adenoidectomy and had evidence of being ultra-rapid metabolizers of codeine due to a CYP2D6 polymorphism. (5.1)

Concomitant Use with Benzodiazepines, CNS Depressants

Concomitant use of opioids with benzodiazepines or other central nervous system (CNS) depressants, including alcohol, may result in profound sedation, respiratory depression, coma, and death [see Warning and Precautions (5.2) Drug Interactions (7.1). Avoid use of opioid cough medications in patients taking benzodiazepines, other CNS depressants, or alcohol.

1 INDICATIONS AND USAGE

CODEINE PHOSPHATE AND CHLORPHENIRAMINE MALEATE is a combination of codeine phosphate, an opiate agonist antitussive, and chlorpheniramine maleate, a histamine-1 (H1) receptor antagonist indicated for the relief of cough and symptoms associated with upper respiratory allergies or a common cold. (1) Important Limitations of Use Not indicated for pediatric patients under 18 years of age (8.4))

2 DOSAGE AND ADMINISTRATION

Adults and children 18 years of age and older: 1 tablet every 12 hours, not to exceed 2 doses in 24 hours. (2.1)

3 DOSAGE FORMS AND STRENGTHS

Extended release (ER) tablet: contains 54.3 mg of codeine phosphate (equivalent to 40 mg of codeine) and 8 mg of chlorpheniramine maleate (equivalent to 5.6 mg of chlorpheniramine). (3)

4 CONTRAINDICATIONS

- Post-operative pain management in children undergoing tonsillectomy and/or adenoidectomy. (4)
- Patients with known hypersensitivity to codeine, chlorpheniramine, or any of the product components of CODEINE PHOSPHATE AND CHLORPHENIRAMINE MALEATE. (4)

5 WARNINGS AND PRECAUTIONS

- Risk of death in ultra-rapid metabolizers: Conversion of codeine into its active metabolite, morphine, may occur more rapidly and completely resulting in higher than expected morphine levels and respiratory depression or death. (5.1)
- Risks using with Benzodiazepines or other CNS Depressants. (5.2)
- Dose-related respiratory depression. Use with caution. (5.3)
- Drug dependence: Prescribe with caution that is appropriate to the use of other opioids. (5.4)
- Head injury, intra-cranial lesions, or increased intracranial pressure: Avoid in patients with head injury, intra-cranial lesions, or increased intracranial pressure. (5.5)
- Activities requiring mental alertness: Avoid engaging in hazardous tasks requiring complete mental alertness such as driving or operating machinery. Avoid concurrent use of alcohol or other central nervous system depressants.. (5.6)
- Prolonged use may cause Obstructive Bowel Disease (5.7)
- Acute abdominal conditions: Use caution in patients with acute abdominal conditions. (5.8)
- Special risk patients: Caution in elderly patients and those with asthma, persistent or chronic cough, hypothyroidism, Addison’s disease, prostatic hypertrophy or urethral stricture. (5.9)

6 ADVERSE REACTIONS

Common adverse reactions of CODEINE PHOSPHATE AND CHLORPHENIRAMINE MALEATE include: Nausea and vomiting, constipation, abdominal distension, abdominal pain, blurred vision, diplopia, visual disturbances, confusion, dizziness, depression, drowsiness, sedation, headache, euphoria, facial dyskinesia, feeling faint, light-headedness, general feeling of discomfort or illness, excitability, nervousness, agitation, restlessness, somnolence, insomnia, dyskinesia, irritability, tremor. (6)

To report SUSPECTED ADVERSE REACTIONS, contact Nexgen Pharma, Inc. at 888-710-0006 or go to www.nexgenpharma.com or FDA at 1-800-FDA-1088

7 DRUG INTERACTIONS

- Opioids, antihistamines, antipsychotics, anti-anxiety agents, or other CNS depressants: may cause additive CNS depression. (7.1)
- MAOIs or tricyclic antidepressants: may increase the effect of either the antidepressant or codeine. (7.2)
- Anticholinergic drugs: Use with caution. Additive adverse effects resulting from cholinergic blockage (e.g., xerostomia, blurred vision, or constipation) may occur. (7.3)
- Inhibitors or inducers of metabolic enzymes: Concomitant use of cytochrome P450 2D6 and 3A4 enzyme inhibitors or inducers may result in an altered response to codeine, monitor antitussive activity. Chlorpheniramine may inhibit the hepatic metabolism of phenytoin, monitor phenytoin toxicity. (7.4)

8 USE IN SPECIFIC POPULATIONS

- Pregnancy: Based on animal data, may cause fetal harm. (8.1)
- Labor: Use of codeine during labor can produce respiratory depression in the neonate. (8.2)
- Nursing mothers: The risk of infant exposure to codeine and morphine through breast milk should be weighed against the benefits of breastfeeding for both the mother and the baby. (8.3)
- Pediatric patients: Safety and effectiveness of this drug product has not been established for patients under 18. (8.4)

FULL PRESCRIBING INFORMATION

WARNINGDEATH RELATED TO ULTRA-RAPID METABOLISM OF CODEINE TO MORPHINE and RISKS FROM CONCOMITANT USE WITH BENZODIAZEPINES OR OTHER CNS DEPRESSANTS

Ultra-Rapid Metabolism

Respiratory depression and death have occurred in children who received codeine following tonsillectomy and/or adenoidectomy and had evidence of being ultra-rapid metabolizers of codeine due to a CYP2D6 polymorphism. (5.1)

Concomitant Use with Benzodiazepines, CNS Depressants

Concomitant use of opioids with benzodiazepines or other central nervous system (CNS) depressants, including alcohol, may result in profound sedation, respiratory depression, coma, and death [see Warning and Precautions (5.2) Drug Interactions (7.1). Avoid use of opioid cough medications in patients taking benzodiazepines, other CNS depressants, or alcohol.

1 INDICATIONS AND USAGE

CODEINE PHOSPHATE AND CHLORPHENIRAMINE MALEATE is indicated for the relief of cough and symptoms associated with upper respiratory allergies or a common cold in adults 18 years of age and older.

Important Limitations of Use

Not indicated for pediatric patients under 18 years of age [see Use in Special Population (8.4)]

2 DOSAGE AND ADMINISTRATION

2.1 Adults 18 Years of Age and Older

CODEINE PHOSPHATE AND CHLORPHENIRAMINE MALEATE should be administered orally at a dosage of one tablet every 12 hours, not to exceed 2 tablets in 24 hours.

3 DOSAGE FORMS AND STRENGTHS

Extended release tablets: Each tablet contains 54.3 mg of codeine phosphate (equivalent to 40 mg of codeine) and 8 mg of chlorpheniramine maleate (equivalent to 5.6 mg of chlorpheniramine). Each tablet is white to off-white, uncoated, round, debossed with NXG on one side and CC on the other side.

4 CONTRAINDICATIONS

CODEINE PHOSPHATE AND CHLORPHENIRAMINE MALEATE is contraindicated in:
Postoperative pain management in children who have undergone tonsillectomy and/or adenoidectomy [see Warnings and Precautions (5.1)].

Patients with known hypersensitivity to codeine, chlorpheniramine or any of the inactive ingredients of CODEINE PHOSPHATE AND CHLORPHENIRAMINE MALEATE. Persons known to be hypersensitive to certain other opioids may exhibit cross-sensitivity to codeine.

5 WARNINGS AND PRECAUTIONS

5.1 Death Related to Ultra-Rapid Metabolism of Codeine to Morphine

Respiratory depression and death have occurred in children who received codeine in the post-operative period following tonsillectomy and/or adenoidectomy and had evidence of being ultra-rapid metabolizers of codeine (i.e., multiple copies of the gene for cytochrome P450 isoenzyme 2D6 or high morphine concentrations). Deaths have also occurred in nursing infants who were exposed to high levels of morphine in breast milk because their mothers were ultra-rapid metabolizers of codeine. [see Use in Specific Populations (8.3)]

Some individuals may be ultra-rapid metabolizers because of a specific CYP2D6 genotype (gene duplications denoted as *1/*1xN or *1/*2xN). The prevalence of this CYP2D6 phenotype varies widely and has been estimated at 0.5 to 1% in Chinese and Japanese, 0.5 to 1% in Hispanics, 1 to 10% in Caucasians, 3% in African Americans, and 16 to 28% in North Africans, Ethiopians, and Arabs. Data are not available for other ethnic groups. These individuals convert codeine into its active metabolite, morphine, more rapidly and completely than other people. This rapid conversion results in higher than expected serum morphine levels. Even at labeled dosage regimens, individuals who are ultra-rapid metabolizers may have life-threatening or fatal respiratory depression or experience signs of overdose (such as extreme sleepiness, confusion, or shallow breathing). [see Overdosage (10)]

Children with obstructive sleep apnea who are treated with codeine for post-tonsillectomy and/or adenoidectomy pain may be particularly sensitive to the respiratory depressant effects of codeine that has been rapidly metabolized to morphine. CODEINE PHOSPHATE AND CHLORPHENIRAMINE MALEATE is contraindicated for post-operative pain management in all pediatric patients undergoing tonsillectomy and/or adenoidectomy [see Contraindications (4)].

When prescribing codeine-containing drugs, healthcare professionals should choose the lowest effective dose for the shortest period of time and inform patients and caregivers about these risks and the signs of morphine overdose. [see Use in Specific Populations (8), Overdosage (10)]

5.2 Risks from Concomitant Use with Benzodiazepines or other CNS Depressants

Concomitant use of opioids, including CODEINE PHOSPHATE AND CHLORPHENIRAMINE MALEATE, with benzodiazepines, or other CNS depressants, including alcohol, may result in profound sedation, respiratory depression, coma, and death. Because of these risks, avoid use of opioid cough medications in patients taking Benzodiazepines, other CNS depressants, or alcohol [see Drug Interactions (7.1)].

Observational studies have demonstrated that concomitant use of opioid analgesics and benzodiazepines increases the risk of drug-related mortality compared to use of opioids alone. Because of similar pharmacologic properties, it is reasonable to expect similar risk with concomitant use of opioid cough medications and benzodiazepines, other CNS depressants, or alcohol.

Advise both patients and caregivers about the risks of respiratory depression and sedation if CODEINE PHOSPHATE AND CHLORPHENIRAMINE MALEATE is used with benzodiazepines, alcohol, or other CNS depressants. [see Patient Counseling Information (17)]

5.3 Respiratory Depression

Codeine, one of the active ingredients in CODEINE PHOSPHATE AND CHLORPHENIRAMINE MALEATE, produces dose-related respiratory depression by directly acting on brain stem respiratory centers.

Overdose of codeine in adults has been associated with fatal respiratory depression, and the use of codeine in children has been associated with fatal respiratory depression. Exercise caution when administering CODEINE PHOSPHATE AND CHLORPHENIRAMINE MALEATE because of the potential for respiratory depression. If respiratory depression occurs, discontinue CODEINE PHOSPHATE AND CHLORPHENIRAMINE MALEATE and use naloxone hydrochloride when indicated to antagonize the effect and other supportive measures as necessary. [see Overdosage (10)].

5.4 Drug Dependence

Codeine can produce drug dependence of the morphine type and, therefore, has the potential for being abused. Psychological dependence, physical dependence, and tolerance may develop upon repeated administration of CODEINE PHOSPHATE AND CHLORPHENIRAMINE MALEATE. Prescribe and administer CODEINE PHOSPHATE AND CHLORPHENIRAMINE MALEATE with the same degree of caution appropriate to the use of other opioid drugs. [see Drug Abuse and Dependence (9.2, 9.3)]

5.5 Head Injury and Increased Intracranial Pressure

The respiratory depression effects of opioids and their capacity to elevate cerebrospinal fluid pressure may be markedly exaggerated in the presence of head injury, other intracranial lesions, or a pre-existing increase in intracranial pressure. Furthermore, opioids produce adverse reactions that may obscure the clinical course of patients with head injuries. The use of CODEINE PHOSPHATE AND CHLORPHENIRAMINE MALEATE should be avoided in these patients.

5.6 Activities Requiring Mental Alertness

Codeine and chlorpheniramine, the active ingredients in CODEINE PHOSPHATE AND CHLORPHENIRAMINE MALEATE, may produce marked drowsiness and impair the mental and/or physical abilities required for the performance of potentially hazardous tasks such as driving a car or operating machinery. Advise patients to avoid engaging in hazardous tasks requiring mental alertness and motor coordination after ingestion of CODEINE PHOSPHATE AND CHLORPHENIRAMINE MALEATE. Concurrent use of CODEINE PHOSPHATE AND CHLORPHENIRAMINE MALEATE with alcohol or other central nervous system depressants should be avoided because additional impairment of central nervous system performance may occur.

5.7 Obstructive Bowel Disease

Chronic use of opioids, including codeine, may result in obstructive bowel disease especially in patients with underlying intestinal motility disorders. Codeine may cause or aggravate constipation. Use with caution in patients with underlying intestinal motility disorders.

5.8 Acute Abdominal Conditions

CODEINE PHOSPHATE AND CHLORPHENIRAMINE MALEATE should be used with caution in patients with acute abdominal conditions since the administration of codeine may obscure the diagnosis or clinical course of patients with acute abdominal conditions. The concurrent use of other anticholinergics with codeine may produce paralytic ileus. [see Drug Interactions (7.3)]

5.9 Special Risk Patients

As with other opioids, CODEINE PHOSPHATE AND CHLORPHENIRAMINE MALEATE should be used with caution in elderly or debilitated patients and those with asthma, persistent or chronic cough, hypothyroidism, Addison's disease, prostatic hypertrophy or urethral stricture. The usual precautions should be observed and the possibility of respiratory depression should be kept in mind.

6 ADVERSE REACTIONS

Use of codeine, an opioid, may result in the following:

- Respiratory depression [see Warnings and Precautions (5.3) and Overdosage (10)]
- Drug dependence [see Warnings and Precautions (5.4)]
- Increased intracranial pressure [see Warnings and Precautions (5.5)]
- Decreased mental alertness with impaired mental and/or physical abilities [see Warnings and Precautions (5.6)]
- Paralytic ileus [see Warnings and Precautions (5.7)]

Use of chlorpheniramine, an antihistamine, may result in:

- Decreased mental alertness with impaired mental and/or physical abilities [see Warnings and Precautions (5.6)]

Adverse reactions listed below have been reported in the literature for codeine and chlorpheniramine and may be expected to occur with CODEINE PHOSPHATE AND CHLORPHENIRAMINE MALEATE. Also included are events that occurred during clinical pharmacokinetic studies (in a total of 66 healthy adult volunteers with either single or multiple dose exposure) with CODEINE PHOSPHATE AND CHLORPHENIRAMINE MALEATE and judged by the investigator to be related to study treatment. Because these reactions may be reported voluntarily from a population of uncertain size, it is not always possible to reliably estimate their frequency or establish a causal relationship to drug exposure.

Allergic: Allergic laryngospasm, nasal stuffiness, bronchospastic allergic reaction, hives, itching, swelling of face.

Body as a whole: Asthenia, feeling of relaxation, redness or flushing of the face, unusual tiredness, weakness. Cardiovascular: Fast, or slow heartbeat, hypertension, hypotension, orthostatic hypotension, palpitations, shock-like state, syncope.

Dermatological System: Skin rash, pruritus, erythema, urticaria, excessive perspiration, dermatitis.

Endocrine System: Changes in glucose utilization, decreased lactation, early menses, glycosuria, gynecomastia, hypoglycemia, increased appetite, increased libido, pheochromocytoma stimulation.

Gastrointestinal System: Nausea and vomiting,, constipation, abdominal distension, abdominal pain, acute pancreatitis, dry mouth, dyspepsia, epigastric distress, loss of appetite, diarrhea, gastro-esophageal reflux, gastrointestinal hypomotility.

Genitourinary System: Ureteral spasm, urinary retention, dysuria, urinary frequency, urinary hesitancy, irritative bladder symptom.

Nervous System: Blurred vision, diplopia, visual disturbances, confusion, dizziness, depression, drowsiness, sedation, headache, euphoria, facial dyskinesia, false sense of well-being, feeling faint, lightheadedness, general feeling of discomfort or illness, excitability nervousness, agitation, restlessness, somnolence, insomnia, dyskinesia, irritability, tremor.

Respiratory: Dryness of the pharynx and respiratory passages, laryngismus, atelectasis, wheezing, troubled breathing, respiratory depression, hiccups.

Special Senses: labyrinthitis, tinnitus, vertigo, hypermetropia, lacrimation increased, mydriasis, photophobia.

7 DRUG INTERACTIONS

7.1 Benzodiazepines, Opioids, Antihistamines, Antipsychotics, Anti-anxiety Agents, or Other CNS Depressants (Including Alcohol)

The use of benzodiazepines, opioids, antihistamines, antipsychotics, anti-anxiety agents, or other CNS depressants (including alcohol) concomitantly with CODEINE PHOSPHATE AND CHLORPHENIRAMINE MALEATE may cause an additive CNS depressant effect, profound sedation, respiratory depression, coma, and death and should be avoided. [see Warnings and Precautions (5.2)].

7.2 Monoamine Oxidase Inhibitors and Tricyclic Antidepressants

Do not prescribe CODEINE PHOSPHATE AND CHLORPHENIRAMINE MALEATE if the patient is taking a monoamine oxidase inhibitor (MAOI) (i.e., certain drugs used for depression, psychiatric or emotional conditions, or Parkinson’s disease), or for 2 weeks after stopping a MAOI drug. The use of MAOIs or tricyclic antidepressants with codeine preparations may increase the effect of either the antidepressant or codeine.

7.3 Anticholinergic Drugs

Codeine and chlorpheniramine should be administered cautiously to persons receiving other anticholinergic drugs in order to avoid paralytic ileus and excessive anticholinergic effects.

Additive adverse effects resulting from cholinergic blockade (e.g., xerostomia, blurred vision, or constipation) may occur when anticholinergic drugs are administered with chlorpheniramine.

7.4 Inhibitors or Inducers of Metabolic Enzymes

Codeine is metabolized by the CYP2D6 and CYP3A4 isoenzymes [see Pharmacokinetics (12.3)]. The concurrent use of drugs that preferentially induce codeine N-demethylation (via CYP3A4) may increase the plasma concentrations of codeine’s inactive metabolite norcodeine. Drugs that inhibit codeine O-demethylation (via CYP2D6), may decrease the plasma concentration of codeine’s active metabolites, morphine and morphine-6-glucuronide. The contribution of these active metabolites to the overall antitussive effect of codeine is not known, but should be considered.

Adverse event reports in the literature suggest a possible drug interaction involving increased serum phenytoin levels and phenytoin toxicity when chlorpheniramine and phenytoin are co-administered. The exact mechanism for this interaction is not known, however it is believed that chlorpheniramine may inhibit the hepatic metabolism of phenytoin. Patients should be monitored for evidence of phenytoin toxicity such as ataxia, hyperreflexia, nystagmus and tremor when these two drugs are co-administered.

8 USE IN SPECIFIC POPULATIONS

8.1 Pregnancy

Teratogenic Effects

Pregnancy Category C

There are no adequate and well-controlled studies of CODEINE PHOSPHATE AND CHLORPHENIRAMINE MALEATE in pregnant women.

Reproductive toxicity studies have not been conducted with CODEINE PHOSPHATE AND CHLORPHENIRAMINE MALEATE; however, studies are available with individual active ingredients or related active ingredients. Because animal reproduction studies are not always predictive of human response, CODEINE PHOSPHATE AND CHLORPHENIRAMINE MALEATE should be used during pregnancy only if the benefit justifies the potential risk to the fetus.

Codeine:

Codeine has embryolethal and fetotoxic effects in rats. In a study in which pregnant rats were dosed throughout organogenesis, a dose approximately 15 times the maximum recommended human daily dose (MRHDD; on a mg/m^2 basis at an oral maternal dose of 120 mg/kg/day) increased resorptions and decreased fetal weight; however, these effects occurred in the presence of maternal toxicity.

In studies in which rabbits and mice were dosed throughout organogenesis, codeine at doses approximately 7 and 35 times the MRHDD (on a mg/m^2 basis at 30 and 600 mg/kg/day, respectively) produced no adverse developmental effects.

Chlorpheniramine:

A retrospective study found a small, but statistically significant, association between maternal use of chlorpheniramine and inguinal hernia and eye or ear anomalies in children. Other retrospective studies have found that the frequency of congenital anomalies, in general, was not increased among offspring of women who took chlorpheniramine during pregnancy. The significance of these findings to the therapeutic use of chlorpheniramine in human pregnancy is not known.

In studies with chlorpheniramine in which pregnant rats and rabbits were dosed throughout organogenesis, oral doses up to approximately 25 and 30times the MRHDD on a mg/m^2 basis, respectively, produced no adverse developmental effects. However, when mice were dosed throughout pregnancy, a dose approximately 9times the MRHDD (on a mg/m^2 basis at an oral maternal dose of 20 mg/kg/day) was embryolethal, and postnatal survival was decreased when dosing was continued after parturition. Embryolethality was also observed when male and female rats were dosed with approximately 9times the MRHDD (on a mg/m^2 basis at an oral parental dose of 10 mg/kg/day) prior to mating.

Nonteratogenic Effects

Codeine:

Babies born to mothers who have been taking opioids regularly prior to delivery will be physically dependent. The withdrawal signs include irritability and excessive crying, tremors, hyperactive reflexes, increased respiratory rate, increased stools, sneezing, yawning, vomiting, and fever. The intensity of the syndrome does not always correlate with the duration of maternal opioid use or dose.

8.2 Lactation

As with all opioids, administration of CODEINE PHOSPHATE AND CHLORPHENIRAMINE MALEATE to the mother shortly before delivery may result in some degree of respiratory depression in the newborn, especially if higher doses are used.

8.3 Females and Males of Reproductive Potential

Caution should be exercised when CODEINE PHOSPHATE AND CHLORPHENIRAMINE MALEATE is administered to nursing mothers. Codeine is secreted into human milk. In women with normal codeine metabolism (normal CYP2D6 activity), the amount of codeine secreted into human milk is low and dose-dependent. However, some women are ultra-rapid metabolizers of codeine. These women achieve higher-than-expected serum levels of codeine's active metabolite, morphine, leading to higher-than-expected levels of morphine in breast milk and potentially dangerously high serum morphine levels in their breastfed infants. Therefore, maternal use of codeine can potentially lead to serious adverse reactions, including death, in nursing infants.

The risk of infant exposure to codeine and morphine through breast milk should be weighed against the benefits of breastfeeding for both the mother and the baby. Caution should be exercised when codeine is administered to a nursing woman. If a codeine containing product is selected, the lowest dose should be prescribed for the shortest period of time to achieve the desired clinical effect. Mothers using codeine should be informed about when to seek immediate medical care and how to identify the signs and symptoms of neonatal toxicity, such as drowsiness or sedation, difficulty breastfeeding, breathing difficulties, and decreased tone, in their baby. Nursing mothers who are ultra-rapid metabolizers may also experience overdose symptoms such as extreme sleepiness, confusion, or shallow breathing. Prescribers should closely monitor mother-infant pairs and notify treating pediatricians about the use of codeine during breast-feeding [see Warnings and Precautions (5.1)].

Chlorpheniramine is excreted in human milk. The clinical significance is unknown; however, the anticholinergic action of chlorpheniramine may suppress lactation if taken prior to nursing.

8.4 Pediatric Use

Safety and effectiveness of CODEINE PHOSPHATE AND CHLORPHENIRAMINE MALEATE in patients under 18 years of age have not been established. The use of codeine in children has been associated with fatal respiratory depression. [see Warnings and Precautions (5.1)].

8.5 Geriatric Use

Clinical efficacy and safety studies have not been conducted with CODEINE PHOSPHATE AND CHLORPHENIRAMINE MALEATE. Other reported clinical experience with the individual active ingredients of CODEINE PHOSPHATE AND CHLORPHENIRAMINE MALEATE did not include sufficient numbers of subjects aged 65 and over to determine whether they respond differently from younger subjects. In general, dose selection for an elderly patient should be made with caution, usually starting at the low end of the dosing range, reflecting the greater frequency of decreased hepatic, renal, or cardiac function, and of concomitant disease or other drug therapy.

8.6 Renal Impairment

Pharmacokinetics of CODEINE PHOSPHATE AND CHLORPHENIRAMINE MALEATE has not been characterized in renal impairment subjects.

Both codeine phosphate and chlorpheniramine maleate are cleared substantially by the kidney. As such, impaired renal function could potentially lead to the risk of decreased clearance and thereby increased retention or systemic levels of both these drugs. CODEINE PHOSPHATE AND CHLORPHENIRAMINE MALEATE should be used with caution in patients with severe renal impairment.

8.7 Hepatic Impairment

Pharmacokinetics of CODEINE PHOSPHATE AND CHLORPHENIRAMINE MALEATE has not been characterized in hepatic impairment subjects. Both codeine and chlorpheniramine maleate are extensively metabolized by liver before elimination from the body. As such, impaired hepatic function could potentially lead to the risk of decreased metabolism and thereby increased systemic levels of both these drugs. CODEINE PHOSPHATE AND CHLORPHENIRAMINE MALEATE should be used with caution in patients with severe hepatic impairment.

9 DRUG ABUSE AND DEPENDENCE

9.1 Controlled Substance

CODEINE PHOSPHATE AND CHLORPHENIRAMINE MALEATE is a Schedule III controlled prescription product containing codeine and should be prescribed and administered with caution.

9.2 Abuse

Codeine can produce drug dependence of the morphine type and therefore, has the potential for being abused. Psychological dependence, physical dependence, and tolerance may develop upon repeated administration of CODEINE PHOSPHATE AND CHLORPHENIRAMINE MALEATE, and it should be prescribed and administered with the same degree of caution appropriate to the use of other opioid drugs.

9.3 Dependence

Psychological dependence, physical dependence, and tolerance may develop upon repeated administration of opioids; therefore, CODEINE PHOSPHATE AND CHLORPHENIRAMINE MALEATE should be prescribed and administered with caution.

Physical dependence, the condition in which continued administration of the drug is required to prevent the appearance of a withdrawal syndrome, assumes clinically significant proportions only after several weeks of continued oral opioid use, although some mild degree of physical dependence may develop after a few days of opioid therapy.

10 OVERDOSAGE

No human overdosage data are available for CODEINE PHOSPHATE AND CHLORPHENIRAMINE MALEATE.

Codeine

Overdosage with codeine is characterized by respiratory depression (a decrease in respiratory rate and/or tidal volume, Cheyne-Stokes respiration, cyanosis), extreme somnolence progressing to stupor or coma, skeletal muscle flaccidity, cold and clammy skin, and sometimes bradycardia and hypotension. In severe overdosage, apnea, circulatory collapse, cardiac arrest, and death may occur.

Codeine may cause miosis, even in total darkness. Pinpoint pupils are a sign of opioid overdose but are not pathognomonic (e.g., pontine lesions of hemorrhagic or ischemic origin may produce similar findings). Marked mydriasis rather than miosis may be seen with hypoxia in overdose situations.

Chlorpheniramine

Manifestations of chlorpheniramine overdosage may vary from central nervous system depression to stimulation. Central toxic effects are characterized by agitation, anxiety, delirium, disorientation, hallucinations, hyperactivity, sedation, and seizures. Severe overdosage may produce coma, medullary paralysis, and death. Peripheral toxicity includes hypertension, tachycardia, dysrhythmias, vasodilation, hyperpyrexia, mydriasis, urinary retention, and diminished gastrointestinal motility. Dry mouth, pharynx, bronchi, and nasal passages may be observed.

Impaired secretion from sweat glands following toxic doses of drugs with anticholinergic side effects may predispose to hyperthermia.

An adult ingested 400 mg chlorpheniramine with no reported serious adverse effects. Toxic psychosis, a possible class effect from overdose of sedating antihistamines, has been reported with accidental overdose of chlorpheniramine.

Treatment of overdosage consists of discontinuation of CODEINE PHOSPHATE AND CHLORPHENIRAMINE MALEATE together with institution of appropriate therapy.

Give primary attention to re-establishment of adequate respiratory exchange through provision of a patent airway and the institution of assisted or controlled ventilation. The opioid antagonist naloxone hydrochloride is a specific antidote for respiratory depression that may result from overdosage or unusual sensitivity to opioids including codeine. Therefore, an appropriate dose of naloxone hydrochloride should be administered, preferably by the intravenous route, simultaneously with efforts at respiratory resuscitation. For further information, see full prescribing information for naloxone hydrochloride. An antagonist should not be administered in the absence of clinically significant respiratory or circulatory depression. Oxygen, intravenous fluids, vasopressors, and other supportive measures should be employed as indicated. Gastric emptying may be useful in removing unabsorbed drug.

Hemodialysis is not routinely used to enhance the elimination of codeine or chlorpheniramine from the body. Urinary excretion of chlorpheniramine is increased when the pH of the urine is acidic; however, acid diuresis is NOT recommended to enhance elimination in overdose, as the risks of acidemia and acute tubular necrosis in patients with rhabdomyolysis far outweigh any potential benefits.

11 DESCRIPTION

CODEINE PHOSPHATE AND CHLORPHENIRAMINE MALEATE are extended release tablets that contain 54.3 mg of codeine phosphate (equivalent to 40 mg of codeine) and 8 mg of chlorpheniramine maleate (equivalent to 5.6 mg of chlorpheniramine)..

Codeine phosphate [morphine3methyl ether phosphate (1:1) (salt)] hemihydrate, is a narcotic analgesic and antitussive. It has the following structural formula:

Chlorpheniramine maleate is 2-pyridinepropanamine, γ-(4-chlorophenyl)-N,N-dimethyl-, (Z)-2-butenedioate (1:1) and has the following chemical structure:

CODEINE PHOSPHATE AND CHLORPHENIRAMINE MALEATE are white to off-white, uncoated, standard round extended release matrix tablets.

Other ingredients: hypromellose, lactose monohydrate, cellulose microcrystalline, polysorbate 80, magnesium stearate, and colloidal silicon dioxide.

12 CLINICAL PHARMACOLOGY

12.1 Mechanism of Action

Codeine: Codeine is a semisynthetic narcotic antitussive and analgesic with multiple actions qualitatively similar to those of morphine. The precise mechanism of action of codeine and other opiates is not known; however, codeine is believed to act centrally on the cough center. In excessive doses, codeine will depress respiration. Codeine can produce miosis, euphoria, and physical and physiological dependence.

Chlorpheniramine: Chlorpheniramine is a propylamine derivative antihistamine (H1-receptor antagonist) of the alkylamine class that also possesses anticholinergic and sedative activity. It prevents released histamine from dilating capillaries and causing edema of the respiratory mucosa.

12.3 Pharmacokinetics

Absorption

Pharmacokinetic (PK) parameters (Mean ± SD) for CODEINE PHOSPHATE AND CHLORPHENIRAMINE MALEATE in fasting, healthy volunteers are shown in the table below.

PK Parameter | Single-dose |  | Multiple-dose (BID for 6.5 days)
 | Codeine; Mean (± SD) | Chlorpheniramine Maleate; Mean (± SD) | Codeine; Mean (± SD) | Chlorpheniramine Maleate; Mean (± SD)
Tmax (h) (Range) | 3 (2-12) | 6 (4-12) | 3 (2-5) | 5 (3-7)
Cmax (ng/mL) | 46 (11) | 9 (3)
AUCinf (ng.h/mL) for single-dose OR AUC12 (ng.h/mL) for multiple-dose | 383 (99) | 312 (137)
Half life (h) | 4 (1) | 21 (7) | Not determined | Not determined

Food Effect

The presence of a high-fat, high-calorie meal did not significantly impact the PK parameters of CODEINE PHOSPHATE AND CHLORPHENIRAMINE MALEATE.

Distribution

Codeine has been reported to have an apparent volume of distribution of approximately 3-6 L/kg, indicating extensive distribution of the drug into tissues. About 7-25% of codeine, reportedly, is bound to plasma proteins. Codeine passes the blood brain barrier and the placental barrier. Small amounts of codeine and its metabolite, morphine, are transferred to human breast milk.

Chlorpheniramine is widely distributed throughout the tissues of the body, including the central nervous system. It reportedly has an apparent steady-state volume of distribution of approximately 3.2 L/kg in adults and children and is about 70% bound to plasma proteins. Chlorpheniramine and its metabolites likely cross the placental barrier and are excreted into human breast milk.

Metabolism

About 70-80% of the administered dose of codeine is metabolized by conjugation with glucuronic acid to codeine-6‑ glucuronide (C6G) and via O-demethylation to morphine (about 5-10%) and N-demethylation to norcodeine (about 10%) respectively. UDP-glucuronosyltransferase (UGT) 2B7 and 2B4 are the major enzymes mediating glucurodination of codeine to C6G. Cytochrome P-450 (CYP) 2D6 and CYP3A4 are the major enzymes mediating O-demethylation and N-demethylation of codeine respectively. Morphine and norcodeine are further metabolized by conjugation with glucuronic acid. Morphine and its M6 glucuronide conjugate are pharmacologically active. Whether C6G has pharmacological activity is unknown. Norcodeine and M3 glucuronide conjugate of morphine are generally not considered to be pharmacologically active.

Chlorpheniramine is rapidly and extensively metabolized via demethylation in the liver, forming mono- and didesmethyl derivatives. Oxidative metabolism of chlorpheniramine is catalyzed by cytochrome P-450 2D6.

Elimination

Approximately 90% of the total dose of codeine is excreted through the kidneys, of which approximately 10% is unchanged codeine. Plasma half-life of codeine was observed to be about 4 hours with CODEINE PHOSPHATE AND CHLORPHENIRAMINE MALEATE.

Chlorpheniramine and its metabolites are primarily excreted through the kidneys, with large individual variation. Urinary excretion depends on urine pH and flow rate. Plasma half-life of chlorpheniramine was observed to be about 21 hours with CODEINE PHOSPHATE AND CHLORPHENIRAMINE MALEATE.

13 NONCLINICAL TOXICOLOGY

13.1 Carcinogenesis, Mutagenesis, Impairment of Fertility

Carcinogenicity, mutagenicity, and reproductive studies have not been conducted with CODEINE PHOSPHATE AND CHLORPHENIRAMINE MALEATE however, published information is available for the active ingredients

Codeine: In 2-year studies in F344/N rats and B6C3F1 mice, codeine showed no evidence of tumorigenicity at dietary doses up to 70 and 400 mg/kg/day, respectively (approximately 9 and 25 times, respectively, the MRHDD dose for adults and children on a mg/m2 basis).

Codeine was not mutagenic in the in vitro bacterial reverse mutation assay or clastogenic in the in vitro Chinese hamster ovary (CHO) cell chromosomal aberration assay.

Fertility studies with codeine have not been conducted.

Chlorpheniramine: In 2-year studies in F344/N rats and B6C3F1 mice, chlorpheniramine maleate showed no evidence of tumorigenicity when administered 5 days/week at oral doses up to 30 and 50 mg/kg/day, respectively (approximately 25 and 20 times, respectively, the MRHDD on a mg/m2 basis).

Chlorpheniramine maleate was not mutagenic in the in vitro bacterial reverse mutation assay or the in vitro mouse lymphoma forward mutation assay. Chlorpheniramine maleate was clastogenic in the in vitro CHO cell chromosomal aberration assay.

Chlorphenirimaleate had no effects on fertility in rats and rabbits at oral doses approximately 25 and 30 times, respectively, the MRHDD on a mg/m2 basis.

14 CLINICAL STUDIES

The efficacy of CODEINE PHOSPHATE AND CHLORPHENIRAMINE MALEATE is based on previously established findings of effectiveness of codeine and chlorpheniramine at the proposed doses.

16 HOW SUPPLIED/STORAGE AND HANDLING

CODEINE PHOSPHATE AND CHLORPHENIRAMINE MALEATE is supplied as white to off-white, uncoated, standard round tablet, debossed with NXG on one side and CC on the other side. Supplied in bottles of 100 tablets: NDC 0722-7184-01.

Store at 20 to 25°C (68 to 77°F) [see USP Controlled Room Temperature]. Dispense in a tight, light-resistant container, as defined in the USP, with a child-resistant closure.

Keep this and all medicine out of reach of children.

17 PATIENT COUNSELING INFORMATION

Advise the patient to read the FDA-approved patient labeling (Medication Guide).

Overdosage: Advise patients not to increase the dose or dosing frequency of CODEINE PHOSPHATE AND CHLORPHENIRAMINE MALEATE because serious adverse events such as respiratory depression may occur with overdosage. [see Warnings and Precautions (5.2); Overdosage (10)]

Interactions with Benzodiazepines and Other Central Nervous System Depressants: Inform patients and caregivers that potentially fatal additive effects may occur if CODEINE PHOSPHATE AND CHLORPHENIRAMINE MALEATE is used with benzodiazepines or other CNS depressants, including alcohol. Because of this risk, patients should avoid concomitant use of CODEINE PHOSPHATE AND CHLORPHENIRAMINE MALEATE with benzodiazepines or other CNS depressants, including alcohol [see Warnings and Precautions (5.3), Drug Interactions (7.1)].

Activities Requiring Mental Alertness: Caution patients that CODEINE PHOSPHATE AND CHLORPHENIRAMINE MALEATE may produce marked drowsiness and impair the mental and/or physical abilities required for the performance of potentially hazardous tasks such as driving a car or operating machinery. [see Warnings and Precautions (5.6)]

Controlled Substance Status/Potential for Abuse and Dependence: Caution patients that CODEINE PHOSPHATE AND CHLORPHENIRAMINE MALEATE contains codeine and can produce drug dependence. [see Abuse and Dependence (9.2, 9.3)].

Manufactured by:

Nexgen Pharma, Inc.

Irvine, CA 92614

(Rev. 1/2017)

Patient Package Insert

MEDICATION GUIDE

CODEINE PHOSPHATE AND CHLORPHENIRAMINE MALEATE

extended release tablets, CIII

What is the most important information I should know about CODEINE PHOSPHATE AND CHLORPHENIRAMINE MALEATE?

- Taking CODEINE PHOSPHATE AND CHLORPHENIRAMINE MALEATE with benzodiazepines, or other central nervous system depressants, including alcohol can cause severe drowsiness, breathing problems (respiratory depression), coma, and death.
- CODEINE PHOSPHATE AND CHLORPHENIRAMINE MALEATE can cause you to be drowsy. Avoid driving a car or operating machinery during treatment with CODEINE PHOSPHATE AND CHLORPHENIRAMINE MALEATE.
- Do not give CODEINE PHOSPHATE AND CHLORPHENIRAMINE MALEATE to a child to treat pain after tonsillectomy or adenoidectomy surgery.
  - When you take CODEINE PHOSPHATE AND CHLORPHENIRAMINE MALEATE, some of it changes into morphine in your body.
  - In some children and adults this happens very quickly, and can cause you to stop breathing and cause death due to an overdose.
- Women who breastfeed should talk to their healthcare provider before taking CODEINE PHOSPHATE AND CHLORPHENIRAMINE MALEATE
  - When you take CODEINE PHOSPHATE AND CHLORPHENIRAMINE MALEATE, some of it changes into morphine in your body.
  - In some women, this happens very quickly. Codeine and morphine pass into your breast milk. A large amount of morphine can cause your baby to die.
- Call your healthcare provider or get emergency medical help right away if anyone taking CODEINE PHOSPHATE AND CHLORPHENIRAMINE MALEATE, or your breastfeeding baby has any of the symptoms listed below:
- increased sleepiness
- difficulty breathing
- limpness
- confusion
- shallow breathing
- your baby has difficulty breastfeeding
- Keep CODEINE PHOSPHATE AND CHLORPHENIRAMINE MALEATE in a safe place away from children. Accidental use by a child is a medical emergency and can cause death. If a child accidentally takes CODEINE PHOSPHATE AND CHLORPHENIRAMINE MALEATE, get emergency help right away.
- CODEINE PHOSPHATE AND CHLORPHENIRAMINE MALEATE can cause serious side effects, including death.
- Take CODEINE PHOSPHATE AND CHLORPHENIRAMINE MALEATE exactly as prescribed by your healthcare provider. If you take the wrong dose of CODEINE PHOSPHATE AND CHLORPHENIRAMINE MALEATE, you could overdose and die.
- It is especially important when you take CODEINE PHOSPHATE AND CHLORPHENIRAMINE MALEATE that you know exactly what dose to take.

What is CODEINE PHOSPHATE AND CHLORPHENIRAMINE MALEATE?

CODEINE PHOSPHATE AND CHLORPHENIRAMINE MALEATE is a prescription medicine used to treat cough and upper respiratory symptoms that you can have with allergies or a common cold. CODEINE PHOSPHATE AND CHLORPHENIRAMINE MALEATE is for adults 18 years and older. CODEINE PHOSPHATE AND CHLORPHENIRAMINE MALEATE contains 2 medicines, codeine and chlorpheniramine. Codeine is a narcotic cough suppressant. Chlorpheniramine is an antihistamine.

CODEINE PHOSPHATE AND CHLORPHENIRAMINE MALEATE is a federal controlled substance (CIII) because it contains codeine that can be abused or lead to dependence. Keep CODEINE PHOSPHATE AND CHLORPHENIRAMINE MALEATE in a safe place to prevent misuse and abuse. Selling or giving away CODEINE PHOSPHATE AND CHLORPHENIRAMINE MALEATE may harm others and is against the law.

CODEINE PHOSPHATE AND CHLORPHENIRAMINE MALEATE is not for children under 18 years of age. It is not known if CODEINE PHOSPHATE AND CHLORPHENIRAMINE MALEATE is safe and effective in children.

Who should not take CODEINE PHOSPHATE AND CHLORPHENIRAMINE MALEATE?

Do not give CODEINE PHOSPHATE AND CHLORPHENIRAMINE MALEATE to a child to treat pain after tonsillectomy or adenoidectomy surgery.

Do not take CODEINE PHOSPHATE AND CHLORPHENIRAMINE MALEATE if you are allergic to any of the ingredients in CODEINE PHOSPHATE AND CHLORPHENIRAMINE MALEATE. See the end of this Medication Guide for a complete list of ingredients in CODEINE PHOSPHATE AND CHLORPHENIRAMINE MALEATE. You may have an increased risk of having an allergic reaction to CODEINE PHOSPHATE AND CHLORPHENIRAMINE MALEATE if you are allergic to certain other opioid medicines.

Before taking CODEINE PHOSPHATE AND CHLORPHENIRAMINE MALEATE, tell your healthcare provider about all of your medical conditions, including if you:

- have a drug dependence•
- have lung or breathing problems
- have had a head injury•
- have pain in your stomach (abdomen)
- have constipation or problems with your intestines
- have prostate problems
- have problems with your urinary tract (urethral stricture)
- plan to have surgery
- abuse alcohol
- have kidney or liver problems
- have thyroid problems, such as hypothyroidism
- have Addison's disease
- are pregnant or plan to become pregnant. It is not known if CODEINE PHOSPHATE AND CHLORPHENIRAMINE MALEATE will harm your unborn baby. You and your healthcare provider should decide if you should take CODEINE PHOSPHATE AND CHLORPHENIRAMINE MALEATE while you are pregnant.
- are breastfeeding or plan to breastfeed. Codeine and chlorpheniramine pass into your breast milk and may harm your baby. You and your healthcare provider should discuss whether you should take CODEINE PHOSPHATE AND CHLORPHENIRAMINE MALEATE or breastfeed. You should not do both.

Tell your healthcare provider about all of the medicines you take, including prescription and over-the-counter medicines, vitamins, and herbal supplements.

Using CODEINE PHOSPHATE AND CHLORPHENIRAMINE MALEATE with certain other medicines may affect each other. Using CODEINE PHOSPHATE AND CHLORPHENIRAMINE MALEATE with other medicines can cause serious side effects.

Especially tell your healthcare provider if you:

- take pain medicines such as narcotics
- take cold or allergy medicines that contain antihistamines or cough suppressants
- take medicines for mental illness (anti-psychotics, anti-anxiety)
- drink alcohol
- take medicines for depression, other mental health problems, or Parkinson's disease, including monoamine oxidase inhibitors (MAOIs), or if you have taken an MAOI in the last 14 days
- take medicines for stomach or intestine problems

Ask your healthcare provider if you are not sure if you take one of these medicines.

How should I take CODEINE PHOSPHATE AND CHLORPHENIRAMINE MALEATE?

- Take CODEINE PHOSPHATE AND CHLORPHENIRAMINE MALEATE exactly as your healthcare provider tells you.
- Do not take more than 2 CODEINE PHOSPHATE AND CHLORPHENIRAMINE MALEATE tablets in 24 hours.
- If you take too much CODEINE PHOSPHATE AND CHLORPHENIRAMINE MALEATE, call your healthcare provider or go to the nearest hospital emergency room right away.

What should I avoid while taking CODEINE PHOSPHATE AND CHLORPHENIRAMINE MALEATE?

- CODEINE PHOSPHATE AND CHLORPHENIRAMINE MALEATE can cause you to be drowsy. Avoid driving a car or using machinery during treatment with CODEINE PHOSPHATE AND CHLORPHENIRAMINE MALEATE.
- Do not drink alcohol during treatment with CODEINE PHOSPHATE AND CHLORPHENIRAMINE MALEATE. Drinking alcohol can increase your chances of having serious side effects.

What are the possible side effects of CODEINE PHOSPHATE AND CHLORPHENIRAMINE MALEATE?

CODEINE PHOSPHATE AND CHLORPHENIRAMINE MALEATE may cause serious side effects, including:

- See “What is the most important information I should know about CODEINE PHOSPHATE AND CHLORPHENIRAMINE MALEATE”
- Breathing problems (respiratory depression) which can lead to death. Call your healthcare provider or get emergency treatment right away if you have excessive sleepiness, shallow or slow breathing, or confusion.
- Physical dependence or abuse. Take CODEINE PHOSPHATE AND CHLORPHENIRAMINE MALEATE exactly as your healthcare provider tells you to take it.
- Stopping CODEINE PHOSPHATE AND CHLORPHENIRAMINE MALEATE suddenly could cause withdrawal symptoms.
- Increased intracranial pressure
- Bowel problems including constipation or stomach pain.

The most common side effects of CODEINE PHOSPHATE AND CHLORPHENIRAMINE MALEATE include:

- nausea and vomiting
- constipation
- swelling or boating of your stomach-area
- stomach-area pain
- vision problems, including blurred vision and double vision
- depression
- drowsiness
- headache
- feeling high (euphoria)
- feeling faint
- light headedness
- general feeling of discomfort or illness
- excitability, nervousness
- agitation, restlessness, irritability
- sleepiness
- difficulty sleeping (insomnia)
- unable to control muscle movements
- tremor

These are not all the possible side effects of CODEINE PHOSPHATE AND CHLORPHENIRAMINE MALEATE.

Call your doctor for medical advice about side effects. You may report side effects to FDA at 1-800-FDA-1088.

How should I store CODEINE PHOSPHATE AND CHLORPHENIRAMINE MALEATE?

- Store CODEINE PHOSPHATE AND CHLORPHENIRAMINE MALEATE in a safe place between 68oF to 77oF (20oC to 25oC).
- Keep CODEINE PHOSPHATE AND CHLORPHENIRAMINE MALEATE in a tightly closed, child-resistant container and out of the light.
- Safely throw away medicine that is out of date or no longer needed.
- Keep CODEINE PHOSPHATE AND CHLORPHENIRAMINE MALEATE and all medicines out of the reach of children.

General information about the safe and effective use of CODEINE PHOSPHATE AND CHLORPHENIRAMINE MALEATE.

Medicines are sometimes prescribed for purposes other than those listed in a Medication Guide. Do not use CODEINE PHOSPHATE AND CHLORPHENIRAMINE MALEATE for a condition for which it was not prescribed. Do not give CODEINE PHOSPHATE AND CHLORPHENIRAMINE MALEATE to other people, even if they have the same symptoms that you have. It may harm them. You can ask your pharmacist or healthcare provider for information about CODEINE PHOSPHATE AND CHLORPHENIRAMINE MALEATE that is written for health professionals.

What are the ingredients in CODEINE PHOSPHATE AND CHLORPHENIRAMINE MALEATE?

Active ingredients: codeine and chlorpheniramine

Inactive ingredients: Hypromellose, lactose monohydrate, cellulose microcrystalline, polysorbate 80, magnesium stearate, and colloidal silicon dioxide.

Manufactured By: Nexgen Pharma, Inc.
Irvine, CA 92614

For more information go to www.nexgenpharma.com or call 888-710-0006

This Medication Guide has been approved by the U.S. Food and Drug Administration Issued: January 2017